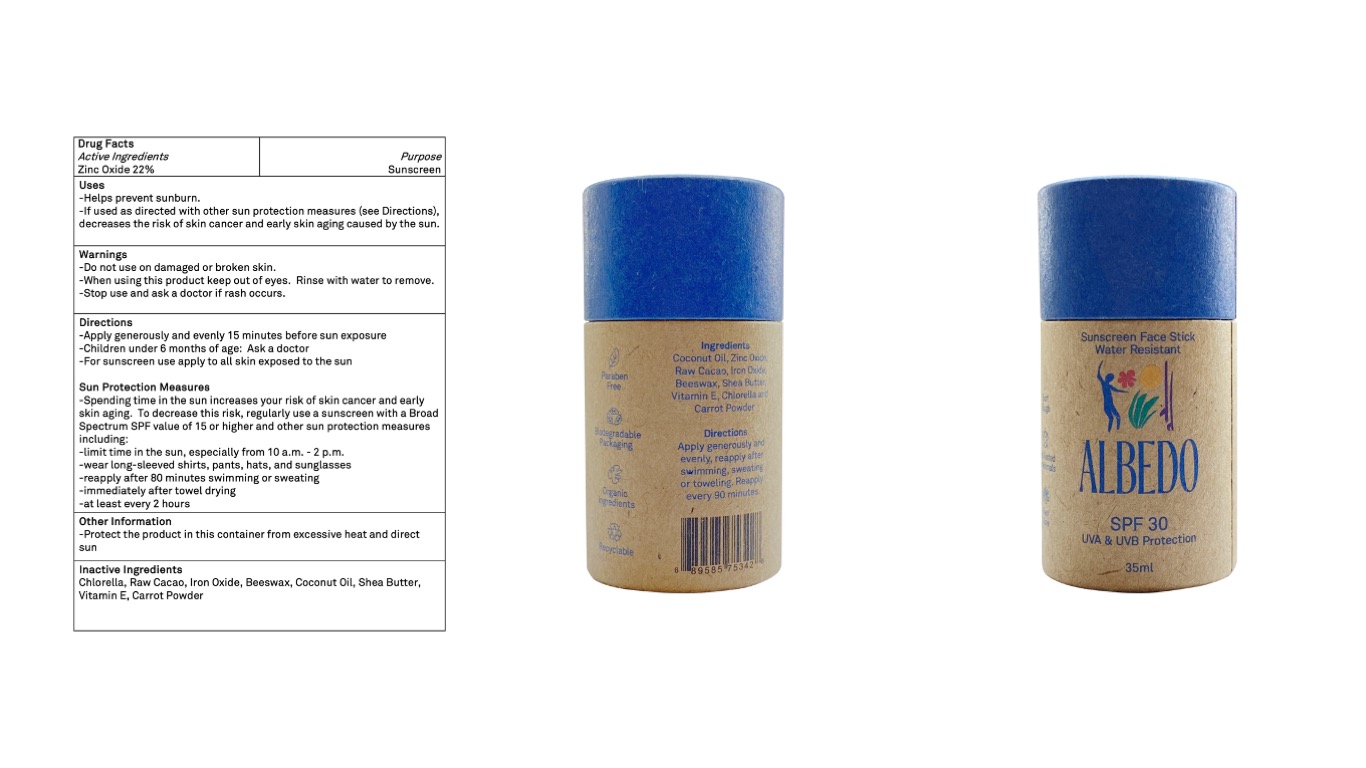 DRUG LABEL: Sunscreen Facestick SPF30
NDC: 81055-000 | Form: LOTION
Manufacturer: Llama Cosmetics LLC
Category: otc | Type: HUMAN OTC DRUG LABEL
Date: 20201106

ACTIVE INGREDIENTS: ZINC OXIDE 22 mg/100 mg
INACTIVE INGREDIENTS: PEG-8 BEESWAX 33 mg/100 mg

This product is manufactured with the ingredients as listed.

Active Ingredient(s)

Zinc Oxide 22%wt

Purpose

Sunscreen

Use

-Helps prevent sunburn.

-If used as directed with other sun protection measures (see Directions), decreases the risk of skin cancer and early skin aging caused by the sun.

Warnings

-When using this product keep out of eyes. Rinse with water to remove.

Do not use

-in children less than 6 months of age

-on open skin wounds

WHEN USING

Use as directed

Stop use and ask a doctor if irritation or rash occurs. These may be signs of a serious condition.

Keep out of reach of children. If swallowed, get medical help or contact a Poison Control Center right away.

Directions

-Apply generously and evenly 15 minutes before sun exposure

-Children under 6 months of age: Ask a doctor

-For sunscreen use apply to all skin exposed to the sun

Sun Protection Measures

-Spending time in the sun increases your risk of skin cancer and early skin aging. To decrease this risk, regularly use a sunscreen with a Broad Spectrum SPF value of 15 or higher and other sun protection measures including:

-limit time in the sun, especially from 10 a.m. - 2 p.m.

-wear long-sleeved shirts, pants, hats, and sunglasses

-reapply after 80 minutes swimming or sweating

-immediately after towel drying

-at least every 2 hours

Other information

-Store at room temperature, avoid large variations in temperature.

-Keep in dry conditions and avoid contact with moisture.

Inactive ingredients

Chlorella, Raw Cacao, Iron Oxide, Beeswax, Coconut Oil, Shea Butter, Vitamin E, Carrot Powder

Albedo SPF 30 FaceStick Sunscreen

SPF 30, Water Resistant 80min, Sunscreen Facestick Packaging